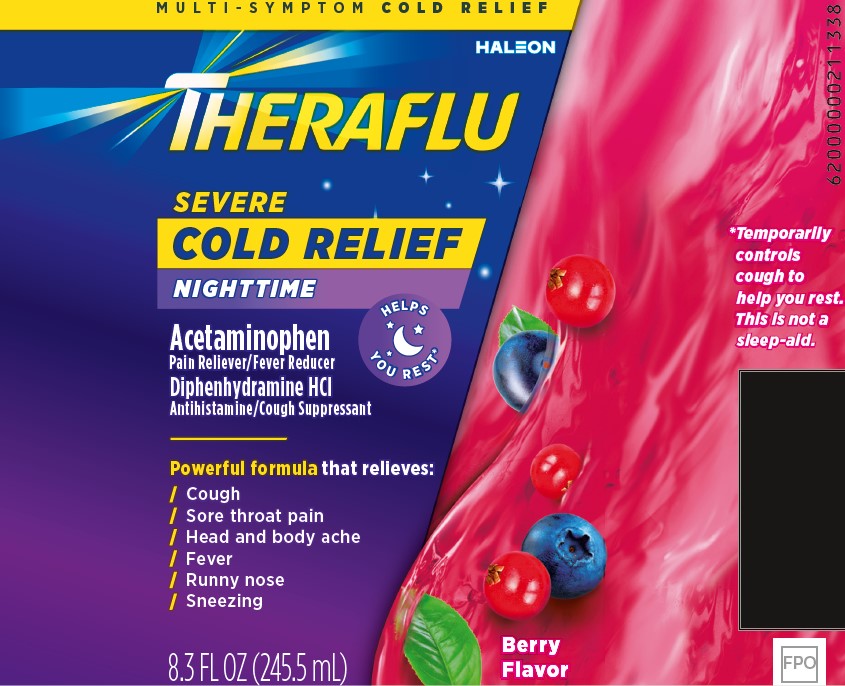 DRUG LABEL: Theraflu

NDC: 0067-0105 | Form: SYRUP
Manufacturer: Haleon US Holdings LLC
Category: otc | Type: HUMAN OTC DRUG LABEL
Date: 20251113

ACTIVE INGREDIENTS: ACETAMINOPHEN 650 mg/30 mL; DIPHENHYDRAMINE HYDROCHLORIDE 25 mg/30 mL
INACTIVE INGREDIENTS: ACESULFAME POTASSIUM; ANHYDROUS CITRIC ACID; EDETATE DISODIUM; FD&C BLUE NO. 1; FD&C RED NO. 40; GLYCERIN; MALTITOL; PROPYLENE GLYCOL; WATER; SODIUM BENZOATE; SODIUM CITRATE, UNSPECIFIED FORM

Drug Facts

Active ingredients (in each 30 mL)

Acetaminophen 650 mg

Diphenhydramine HCl 25 mg

Purposes

Pain reliever/Fever reducer

Antihistamine/Cough suppressant

Uses

- temporarily relieves these symptoms to a cold:
  - minor aches and pains
  - minor sore throat pain
  - headache
  - runny nose
  - sneezing
  - itchy nose or throat
  - itchy, watery eyes due to hay fever
  - cough due to minor throat and bronchial irritation
- temporarily reduces fever

Warnings

Liver warning:This product contains acetaminophen. Severe liver damage may occur if you take

- more than 4,000 mg of acetaminophen in 24 hours
- with other drugs containing acetaminophen
- 3 or more alcoholic drinks every day while using this product

Allergy alert:Acetaminophen may cause severe skin reactions. Symptoms may include:

- skin reddening
- blisters
- rash

If a skin reaction occurs, stop use and seek medical help right away.

Sore throat warning:If sore throat is severe, persists for more than 2 days, is accompanied or followed by fever, headache, rash, nausea, or vomiting consult a doctor promptly.

Do not use

- in a child under 12 years of age
- if you are allergic to acetaminophen
- with any other drug containing acetaminophen (prescription or nonprescription). If you are not sure whether a drug contains acetaminophen, ask a doctor or pharmacist.
- with any other product containing diphenhydramine, even one used on the skin
- to sedate a child or make a child sleepy

Ask a doctor before use if you have

- liver disease
- glaucoma
- trouble urinating due to an enlarged prostate gland
- a breathing problem such as emphysema or chronic bronchitis
- cough that occurs with too much phlegm (mucus)
- cough that lasts or is chronic such as occurs with smoking, asthma, or emphysema

Ask a doctor or pharmacist before use if you are

- taking sedatives or tranquilizers
- taking the blood thinning drug warfarin

When using this product

- avoid alcoholic drinks
- marked drowsiness may occur
- alcohol, sedatives and tranquilizers may increase drowsiness
- be careful when driving a motor vehicle or operating machinery
- excitability may occur, especially in children

Stop use and ask a doctor if

- fever gets worse or lasts more than 3 days
- redness or swelling is present
- new symptoms occur
- pain or cough gets worse or lasts more than 7 days
- cough comes back or occurs with rash or headache that lasts

These could be signs of a serious condition.

If pregnant or breast-feeding,

ask a health professional before use.

Keep out of reach of children.

In case of overdose, get medical help or contact a Poison Control Center right away. Prompt medical attention is critical for adults as well as for children even if you do not notice any signs or symptoms.

Directions

- do not use more than directed
- measure the dose correctly using the enclosed dosing cup
- take every 4 hours in dosing cup provided, while symptoms persist
- do not take more than 5 doses (150 mL) in 24 hours unless directed by a doctor

Age | Dose
Adults and children 12 years of age and over | 30 mL
Children under 12 years of age | do not use

Other information

- each 30 mL contains:potassium 30 mg, sodium 13 mg
- store at controlled room temperature 20°-25°C (68° – 77°F)

Inactive ingredients

acesulfame potassium, anhydrous citric acid, edetate disodium, FD&C blue no. 1, FD&C red no. 40, glycerin, maltitol solution, natural and artificial flavors, propylene glycol, purified water, sodium benzoate, sodium citrate

Questions or comments?

1-855-328-5259

Other Information

Distributed by: Haleon, Warren, NJ 07059 Made in Mexico Trademarks are owned by or licensed to the Haleon group of companies. ©2024 Haleon group of companies or its licensor. Pat. Info www.productpats.com

PEEL BACK HERE

DO NOT USE IF NECKBAND PRINTED WITH “SEALED FOR SAFETY” IS TORN OR MISSING.

Package/Label Principal Display Panel

MULTI-SYMPTOM COLD RELIEF

THERAFLU

SEVERE

COLD RELIEF

NIGHTTIME

Acetaminophen

Pain Reliever/Fever Reducer

Diphenhydramine HCl

Antihistamine/Cough Suppressant

HELPS YOU REST*

Powerful formula that relieves:

/ Cough

/ Sore throat pain

/ Head and body ache

/ Fever

/ Runny nose

/ Sneezing

8.3 FL OZ (245.5 mL)

Berry Flavor

*Temporarily controls cough to help you rest. This is not a sleep-aid.